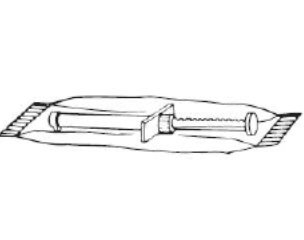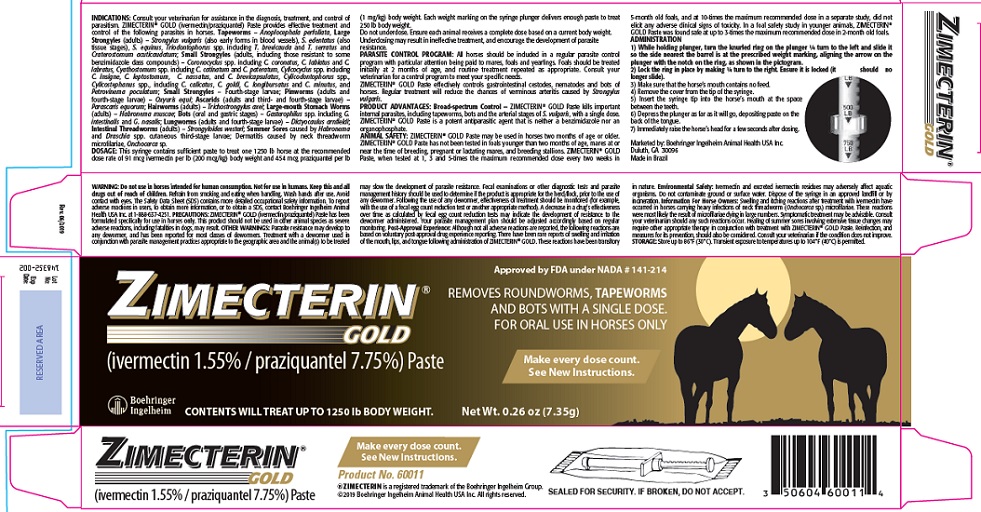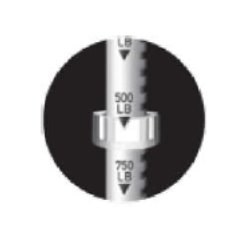 DRUG LABEL: ZIMECTERIN GOLD
NDC: 0010-6001 | Form: PASTE
Manufacturer: Boehringer Ingelheim Animal Health USA Inc.
Category: animal | Type: OTC ANIMAL DRUG LABEL
Date: 20231027

ACTIVE INGREDIENTS: ivermectin 15.5 mg/1 g; praziquantel 77.5 mg/1 g

ZIMECTERIN® GOLD
(ivermectin 1.55% / praziquantel 7.75%) Paste

INDICATIONS:

Consult your veterinarian for assistance in the diagnosis, treatment, and control of parasitism. ZIMECTERIN® GOLD (ivermectin/praziquantel) Paste provides effective treatment and control of the following parasites in horses. Tapeworms – Anoplocephala perfoliata, Large Strongyles (adults) – Strongylus vulgaris (also early forms in blood vessels), S. edentatus (also tissue stages), S. equinus, Triodontophorus spp. including T. brevicauda and T. serratus and Craterostomum acuticaudatum; Small Strongyles (adults, including those resistant to some benzimidazole class compounds) – Coronocyclus spp. including C. coronatus, C. labiatus and C. labratus, Cyathostomum spp. including C. catinatum and C. pateratum, Cylicocyclus spp. including C. insigne, C. leptostomum, C. nassatus, and C. brevicapsulatus, Cylicodontophorus spp., Cylicostephanus spp., including C. calicatus, C. goldi, C. longibursatus and C. minutus, and Petrovinema poculatum; Small Strongyles – Fourth-stage larvae; Pinworms (adults and fourth-stage larvae) – Oxyuris equi; Ascarids (adults and third- and fourth-stage larvae) – Parascaris equorum; Hairworms (adults) – Trichostrongylus axei; Large-mouth Stomach Worms (adults) – Habronema muscae; Bots (oral and gastric stages) – Gasterophilus spp. including G. intestinalis and G. nasalis; Lungworms (adults and fourth-stage larvae) – Dictyocaulus arnfieldi; Intestinal Threadworms (adults) – Strongyloides westeri; Summer Sores caused by Habronema and Draschia spp. cutaneous third-stage larvae; Dermatitis caused by neck threadworm microfilariae, Onchocerca sp.

DOSAGE:

This syringe contains sufficient paste to treat one 1250 lb horse at the recommended dose rate of 91 mcg ivermectin per lb (200 mcg/kg) body weight and 454 mcg praziquantel per lb (1 mg/kg) body weight. Each weight marking on the syringe plunger delivers enough paste to treat 250 lb body weight.

Do not underdose. Ensure each animal receives a complete dose based on a current body weight. Underdosing may result in ineffective treatment, and encourage the development of parasite resistance.

PARASITE CONTROL PROGRAM:

All horses should be included in a regular parasite control program with particular attention being paid to mares, foals and yearlings. Foals should be treated initially at 2 months of age, and routine treatment repeated as appropriate. Consult your veterinarian for a control program to meet your specific needs.

ZIMECTERIN® GOLD Paste effectively controls gastrointestinal cestodes, nematodes and bots of horses. Regular treatment will reduce the chances of verminous arteritis caused by Strongylus vulgaris.

PRODUCT ADVANTAGES: Broad-spectrum Control

ZIMECTERIN® GOLD Paste kills important internal parasites, including tapeworms, bots and the arterial stages of S. vulgaris, with a single dose. ZIMECTERIN® GOLD Paste is a potent antiparasitic agent that is neither a benzimidazole nor an organophosphate.

ANIMAL SAFETY:

ZIMECTERIN® GOLD Paste may be used in horses two months of age or older. ZIMECTERIN® GOLD Paste has not been tested in foals younger than two months of age, mares at or near the time of breeding, pregnant or lactating mares, and breeding stallions. ZIMECTERIN® GOLD Paste, when tested at 1, 3 and 5-times the maximum recommended dose every two weeks in 5-month old foals, and at 10-times the maximum recommended dose in a separate study, did not elicit any adverse clinical signs of toxicity. In a foal safety study in younger animals, ZIMECTERIN® GOLD Paste was found safe at up to 3-times the maximum recommended dose in 2-month old foals.

ADMINISTRATION:

1) While holding plunger, turn the knurled ring on the plunger ¼ turn to the left and slide it so the side nearest the barrel is at the prescribed weight marking, aligning the arrow on the plunger with the notch on the ring, as shown in the pictogram.

2) Lock the ring in place by making ¼ turn to the right. Ensure it is locked (it should no longer slide).

3) Make sure that the horse's mouth contains no feed.
4) Remove the cover from the tip of the syringe.
5) Insert the syringe tip into the horse's mouth at the space between the teeth.
6) Depress the plunger as far as it will go, depositing paste on the back of the tongue.
7) Immediately raise the horse's head for a few seconds after dosing.

WARNING:

Do not use in horses intended for human consumption.

Not for use in humans. Keep this and all drugs out of reach of children.

Refrain from smoking and eating when handling. Wash hands after use. Avoid contact with eyes. The Safety Data Sheet (SDS) contains more detailed occupational safety information. To report adverse reactions in users, to obtain more information, or to obtain a SDS, contact Boehringer Ingelheim Animal Health USA Inc. at 1-888-637-4251.

PRECAUTIONS:

ZIMECTERIN® GOLD (ivermectin/praziquantel) Paste has been formulated specifically for use in horses only. This product should not be used in other animal species as severe adverse reactions, including fatalities in dogs, may result.

OTHER WARNINGS:

Parasite resistance may develop to any dewormer, and has been reported for most classes of dewormers.

Treatment with a dewormer used in conjunction with parasite management practices appropriate to the geographic area and the animal(s) to be treated may slow the development of parasite resistance.

Fecal examinations or other diagnostic tests and parasite management history should be used to determine if the product is appropriate for the herd/flock, prior to the use of any dewormer. Following the use of any dewormer, effectiveness of treatment should be monitored (for example, with the use of a fecal egg count reduction test or another appropriate method).

A decrease in a drug's effectiveness over time as calculated by fecal egg count reduction tests may indicate the development of resistance to the dewormer administered. Your parasite management plan should be adjusted accordingly based on regular monitoring.

Post-Approval Experience:

Although not all adverse reactions are reported, the following reactions are based on voluntary post-approval drug experience reporting. There have been rare reports of swelling and irritation of the mouth, lips, and tongue following administration of ZIMECTERIN® GOLD. These reactions have been transitory in nature

Environmental Safety:

Ivermectin and excreted ivermectin residues may adversely affect aquatic organisms. Do not contaminate ground or surface water. Dispose of the syringe in an approved landfill or by incineration.

Information For Horse Owners:

Swelling and itching reactions after treatment with ivermectin have occurred in horses carrying heavy infections of neck threadworm (Onchocerca sp.) microfilariae. These reactions were most likely the result of microfilariae dying in large numbers. Symptomatic treatment may be advisable. Consult your veterinarian should any such reactions occur. Healing of summer sores involving extensive tissue changes may require other appropriate therapy in conjunction with treatment with ZIMECTERIN® GOLD Paste. Reinfection, and measures for its prevention, should also be considered. Consult your veterinarian if the condition does not improve.

STORAGE:

Store up to 86°F (30°C). Transient exposure to temperatures up to 104°F (40°C) is permitted.

Make every dose count.
See New Instructions.

Product No. 60011

®ZIMECTERIN is a registered trademark of the Boehringer Ingelheim Group.
©2019 Boehringer Ingelheim Animal Health USA Inc. All rights reserved.

Marketed by: Boehringer Ingelheim Animal Health USA Inc.

Duluth, GA - 30096
Made in Brazil

SEALED FOR SECURITY. IF BROKEN, DO NOT ACCEPT.

Principal Display Panel – 7.35 g Paste Syringe Carton

Approved by FDA under NADA # 141-214

ZIMECTERIN® GOLD
(ivermectin 1.55% / praziquantel 7.75%) Paste

REMOVES ROUNDWORMS, TAPEWORMS AND BOTS WITH A SINGLE DOSE.
FOR ORAL USE IN HORSES ONLY

Make every dose count.
See New Instructions.

CONTENTS WILL TREAT UP TO 1250 lb BODY WEIGHT.

Net Wt. 0.26 oz (7.35g)